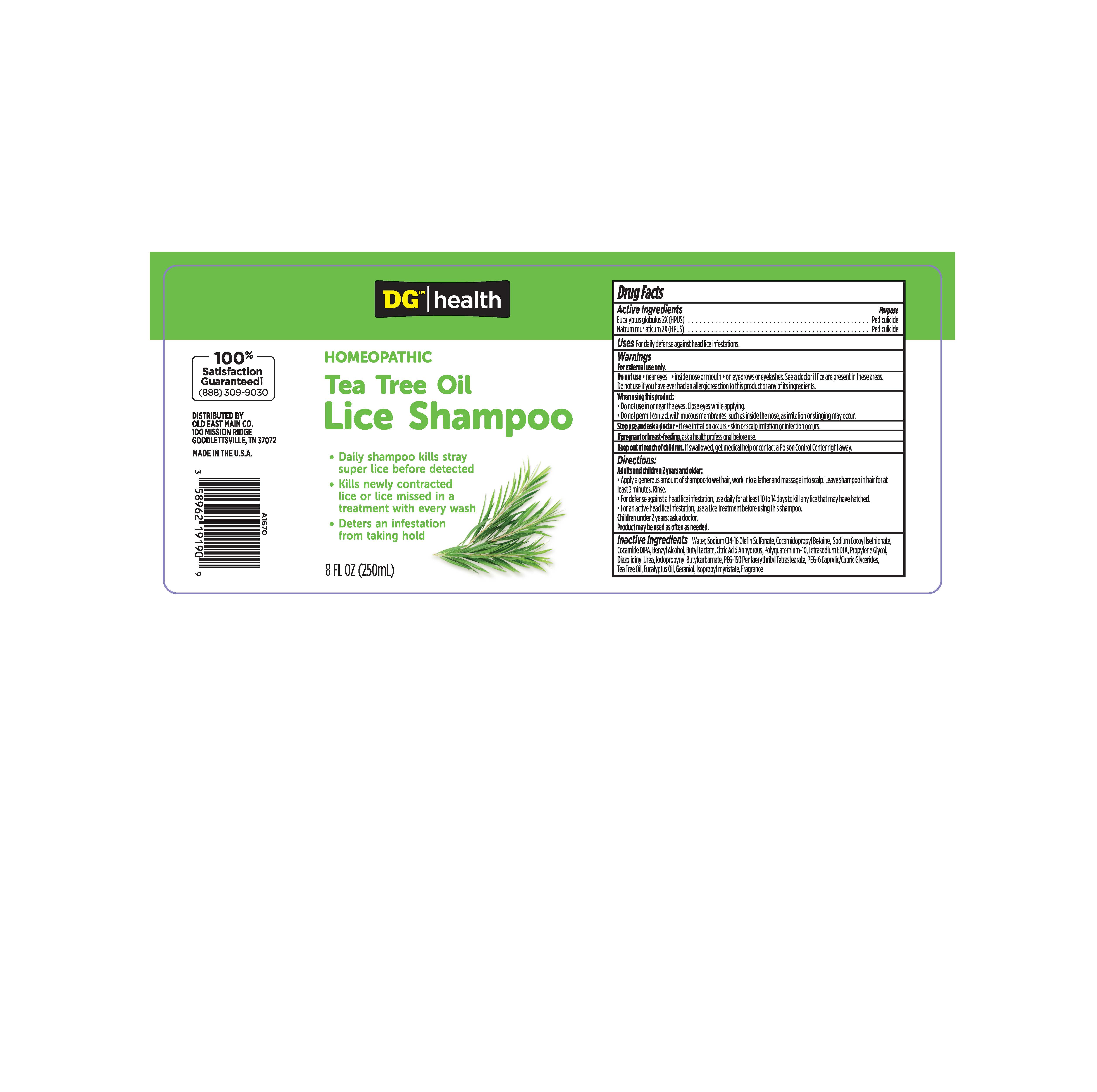 DRUG LABEL: Homeopathic Tea Tree Oil Lice
NDC: 44038-0192 | Form: SHAMPOO
Manufacturer: Accupac, LLC
Category: homeopathic | Type: HUMAN OTC DRUG LABEL
Date: 20240102

ACTIVE INGREDIENTS: SODIUM CHLORIDE 2 [hp_X]/1 mL; EUCALYPTUS GLOBULUS LEAF 2 [hp_X]/1 mL
INACTIVE INGREDIENTS: EUCALYPTUS OIL; ANHYDROUS CITRIC ACID; IODOPROPYNYL BUTYLCARBAMATE; DIAZOLIDINYL UREA; POLYQUATERNIUM-10 (125 MPA.S AT 2%); COCO DIISOPROPANOLAMIDE; WATER; PEG-150 PENTAERYTHRITYL TETRASTEARATE; BENZYL ALCOHOL; BUTYL LACTATE; ISOPROPYL MYRISTATE; SODIUM C14-16 OLEFIN SULFONATE; PROPYLENE GLYCOL; COCAMIDOPROPYL BETAINE; SODIUM COCOYL ISETHIONATE; CAPRYLOCAPROYL POLYOXYLGLYCERIDES 6; EDETATE SODIUM; GERANIOL; TEA TREE OIL

Active Ingedients

Eucalyptus globulus 2X (HPUS)

Natrum muriaticum 2X (HPUS)

Purpose

Pediculicide

Uses

For daily defense against head lice infestations.

Warnings

For External use only.

Do not use

Near eyes
Inside nose or mouth
On eyebrows or eyelashes. See a doctor if lice are present in these areas. Do not use if you have ever had an allergic reaction to this product or any of its ingredients.

When using this product:

Do not use in or near eyes. Close eyes while applying.
Do not permit contact with mucous membranes, such as inside the nose, as irritation or stinging may occur.

Stop use and ask a doctor

If eye irritation occurs
Skin or scalp irritation or infection occurs.

If pregnant or breast-feeding, ask a health professional before use.

KEEP OUT OF REACH OF CHILDREN

If swallowed, get medical help or contact a Poison Control Center right away.

Directions

Adults and children 2 years and older:

Apply generous amount of shampoo to wet hair, work into a lather and massage into scalp. Leave shampoo in hair for at least 3 minutes. Rinse.
For defense against a head lice infestation, use daily for at least 10 to 14 days to kill any lice that may have hatched.
For an active head lice infestation, use Vamousse Lice Treatment before using this shampoo.

Children under 2 years: ask a doctor.

Product may be used as often as needed.

Inactive Ingredients

Inactive Ingredients Water, Sodium C14-16 Olefin Sulfonate, Cocamidopropyl Betaine, Sodium Cocoyl Isethionate, Cocamide DIPA, Benzyl Alcohol, Butyl Lactate, Citric Acid Anhydrous, Polyquaternium-10, Tetrasodium EDTA, Propylene Glycol, Diazolidinyl Urea, Iodopropynyl Butylcarbamate, PEG-150 Pentaerythrityl Tetrastearate, PEG-6 Caprylic/Capric Glycerides, Tea Tree Oil, Eucalyptus Oil, Geraniol, Isopropyl myristate, Fragrance.

DG Health

Homeopathic

Tea Tree Oil

Lice Shampoo

Daily shampoo kills stray super lice before detected
Kills newly contracted lice or lice missed in a treatment with every wash
Deters and infestation from taking hold
100% Satisfaction Guaranteed!

(888)309-9030

Distributed by

Old East Main Co.

100 Mission Ridge

Goodlettsville, TN 37072

Made in the U.S.A